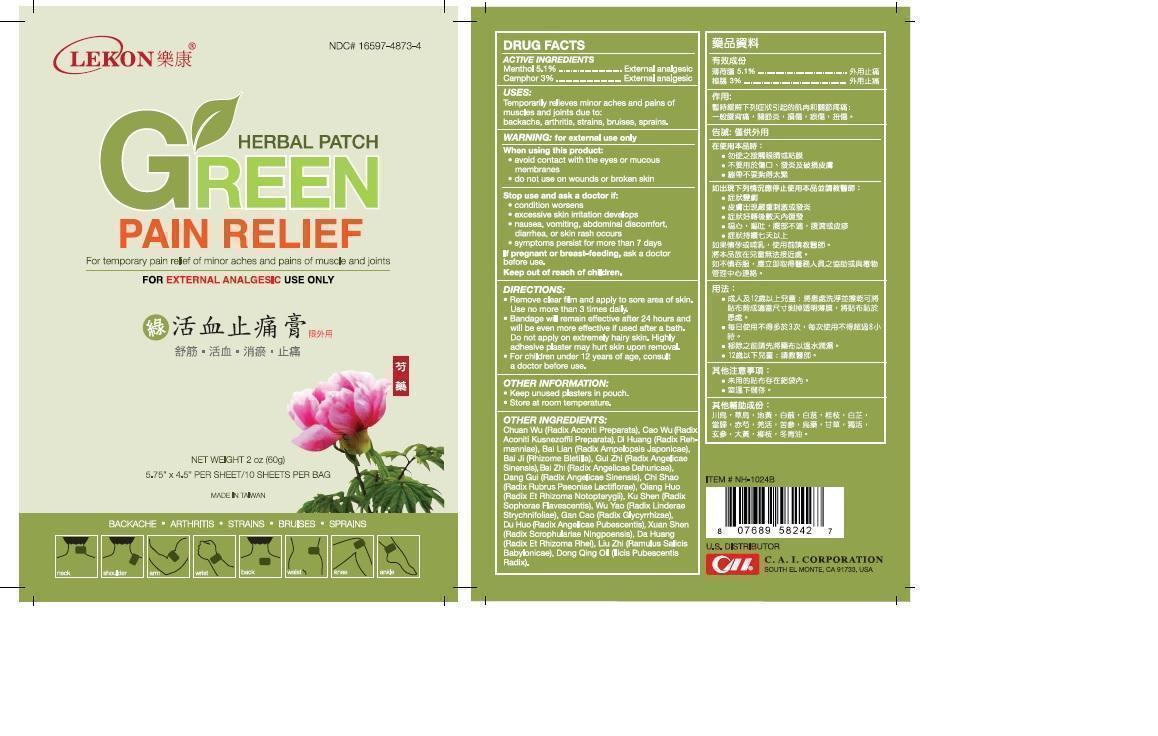 DRUG LABEL: Lekon Herbal Patch Green
NDC: 16597-4873 | Form: PATCH
Manufacturer: Taiwan Three Mast Pharmaceutical Company Limited
Category: otc | Type: HUMAN OTC DRUG LABEL
Date: 20141229

ACTIVE INGREDIENTS: MENTHOL 5.1 g/100 g; CAMPHOR (SYNTHETIC) 3 g/100 g
INACTIVE INGREDIENTS: ACONITUM CARMICHAELII ROOT; ACONITUM KUSNEZOFFII ROOT; REHMANNIA GLUTINOSA ROOT; AMPELOPSIS JAPONICA ROOT; BLETILLA STRIATA BULB; ANGELICA SINENSIS ROOT; ANGELICA DAHURICA ROOT; PAEONIA LACTIFLORA ROOT; NOTOPTERYGIUM FRANCHETII ROOT; SOPHORA FLAVESCENS ROOT; LINDERA AGGREGATA ROOT; LICORICE; ANGELICA PUBESCENS ROOT; SCROPHULARIA NINGPOENSIS ROOT; RHEUM OFFICINALE ROOT; SALIX BABYLONICA WHOLE; ILEX PUBESCENS ROOT

Lekon Herbal Patch Green

ACTIVE INGREDIENTS:

Menthol 5.1%
Camphor 3%

PURPOSE

External analgesic

Keep out of reach of children.

USES:

Temporarily relieves minor aches and pains of muscles and joints due to: backache, arthritis, strains, bruises, sprains.

WARNINGS

WARNING: for external use only
When using this product:
• avoid contact with the eyes or mucous membranes
• do not use on wounds or broken skin
Stop use and ask a doctor if:
• condition worsens
• excessive skin irritation develops
• nausea, vomiting, abdominal discomfort, diarrhea, or skin rash occurs
• symptoms persist for more than 7 days
If pregnant or breast-feeding, ask a doctor before use.

DIRECTIONS:

• Remove clear film and apply to sore area of skin.
Use no more than 3times daily.
• Bandage will remain effective after 24 hours and will be even more effective if used after a bath. Do not apply on extremely hairy skin. Highly adhesive plaster may hurt skin upon removal.
• For children under 12 years of age, consult a doctor before use.

OTHER INGREDIENTS:

Chuan Wu (Radix Aconiti Preparata), Cao Wu (Radix Aconiti Kusnezoffii Preparata), Di Huang (Radix Rehmanniae), Bai Lain (Radix Ampelopsis Japonicae), Bai ji(Rhizome Bletilla), Gui Zhi(Radix Angelicae Sinesis), Bai zhi(Radix Angelicae Dahuricae), Dang Gui(Radix Angelicae Sinesis), Chi Shao (Radix Rubrus Paeoniae Lactiflorae), Qiang Huo (Radix Et Rhizoma Notopterygii), Ku Shen(Radix Sophorae Flavescentis), Wu yao (Radix Linderae Strychnifoliae), Gan Cao (Radix Glycyrrhizae), Du Huo (Radix Angelicae Pubescentis), Xuan Shen(Radix Scrophulariae Ningpoensis), Da Huang (Radix Et Rhizoma Rhei), Liu Zhi (Ramulus Salicis Babylonicae), Dong Qing Oil (LLicis Pubescentis Radix).

OTHER INFORMATION:

• Keep unused plasters in pouch.
• Store at room temperature.